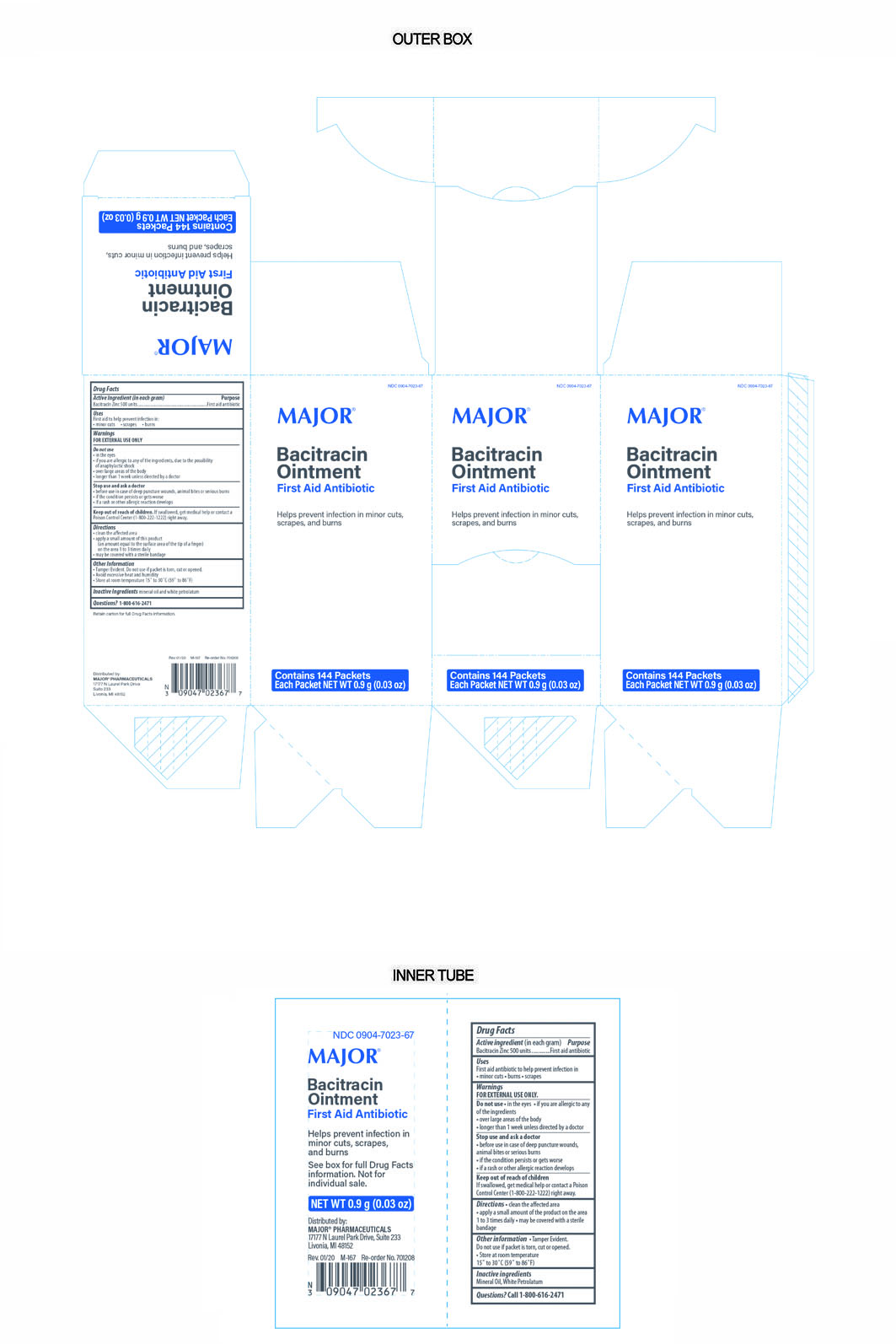 DRUG LABEL: Major Bacitracin
NDC: 0904-7023 | Form: OINTMENT
Manufacturer: Major Pharmaceuticals
Category: otc | Type: HUMAN OTC DRUG LABEL
Date: 20241217

ACTIVE INGREDIENTS: BACITRACIN ZINC 500 [USP'U]/1 g
INACTIVE INGREDIENTS: PETROLATUM; MINERAL OIL

Major Bacitracin Ointment

Active Ingredient

Bacitracin Zinc 500 Units per gram

Purpose

First Aid Antibiotic

Uses

First Aid to help prevent infection in

- minor cuts
- scrapes
- burns

Warnings

For External Use Only.

Do Not Use

- in eyes
- over large areas of the body
- if you are allergic to any of the ingredients, due to the possiblity of anaphylactic shock
- longer than 1 week unless directed by a doctor

Ask Doctor before Use

In care of deep puncture wounds, animal bites, or serious burns.

Stop Use and Ask Doctor if

- Before use in case of deep puncture wounds, animal bites or serious burns
- The condition persists or gets worse
- A rash or allergic reaction develops

Directions

- Clean the affected area
- Apply a small amount of the product (an amount equal to the surface area of the tip of a finger) on the area 1 to 3 times daily
- May be covered with a sterile bandage

Inactive Ingredients

mineral oil, white petrolatum

Questions

Call 1-800-616-2471

Storage Information

Avoid excessive heat and humidity

Store at room temperature 15° to 30°C (59° to 86°F).

Keep out of reach of children

If swallowed, get medical help or contact a Poison Control Center (1-800-222-1222) right away.

Other Information

Tamper evident. Do not use if packet is torn, cut or opened.

Distributed By:

MAJOR® PHARMACEUTICALS

17177 N Laurel Park Drive

Suite 233

Livonia, MI 48152

Product of USA